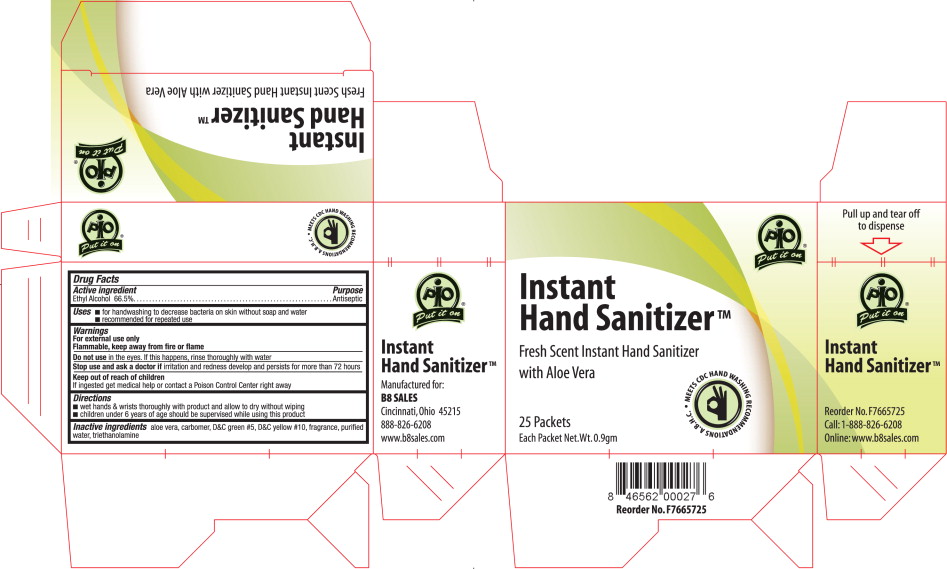 DRUG LABEL: Instant Hand Sanitizer
NDC: 50607-1111 | Form: GEL
Manufacturer: B8 Sales, Inc.
Category: otc | Type: HUMAN OTC DRUG LABEL
Date: 20100402

ACTIVE INGREDIENTS: alcohol .60 g/.9 g
INACTIVE INGREDIENTS: Aloe; D&C Green no. 5; D&C Yellow no. 10; water

PIO
Put it on®

Instant Hand SanitizerTM

Fresh Scent Instant Hand Sanitizer with Aloe Vera

- MEETS CDC HAND WASHING RECOMMENDATIONS A.B.H.C.

25 Packets

Each Packet Net.Wt.0.9gm

Active ingredient

Ethyl Alcohol 66.5%

Purpose

Antiseptic

Uses

- for handwashing to decrease bacteria on skin without soap and water
- recommended for repeated use

Warnings

For external use only

Flammable, keep away from fire or flame

Do not use in the eyes. If this happens, rinse thoroughly with water

Stop use and ask a doctor if irritation and redness develop and persists for more than 72 hours

Keep out of reach of children

If ingested get medical help or contact a Poison Control Center right away

Directions

- wet hands & wrists thoroughly with product and allow to dry without wiping
- children under 6 years of age should be supervised while using this product

Inactive ingredients

aloe vera, carbomer, D&C green #5, DSC yellow #10, fragrance, purified water, triethanolamine

Principal Display Panel

Instant Hand Sanitizer – Carton Label

PIO

Put it on®

Instant Hand SanitizerTM

Fresh Scent Instant Hand Sanitizer with Aloe Vera

- MEETS CDC HAND WASHING RECOMMENDATIONS A.B.H.C.

25 Packets

Each Packet Net.Wt.0.9gm